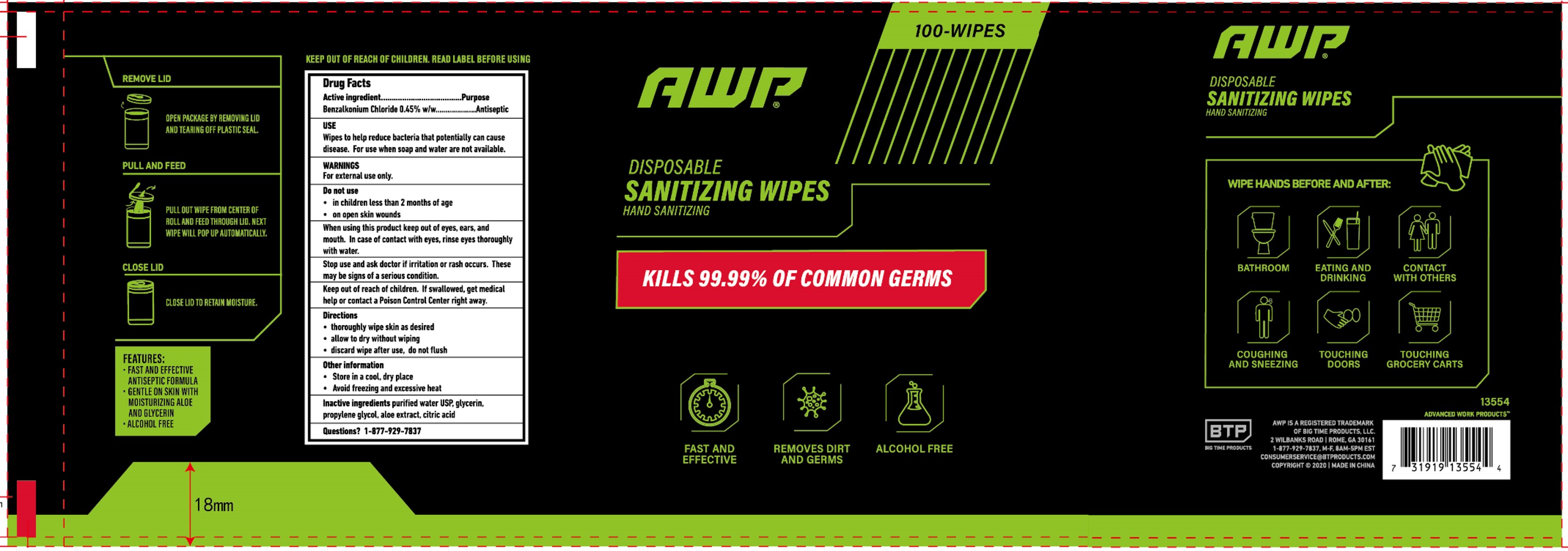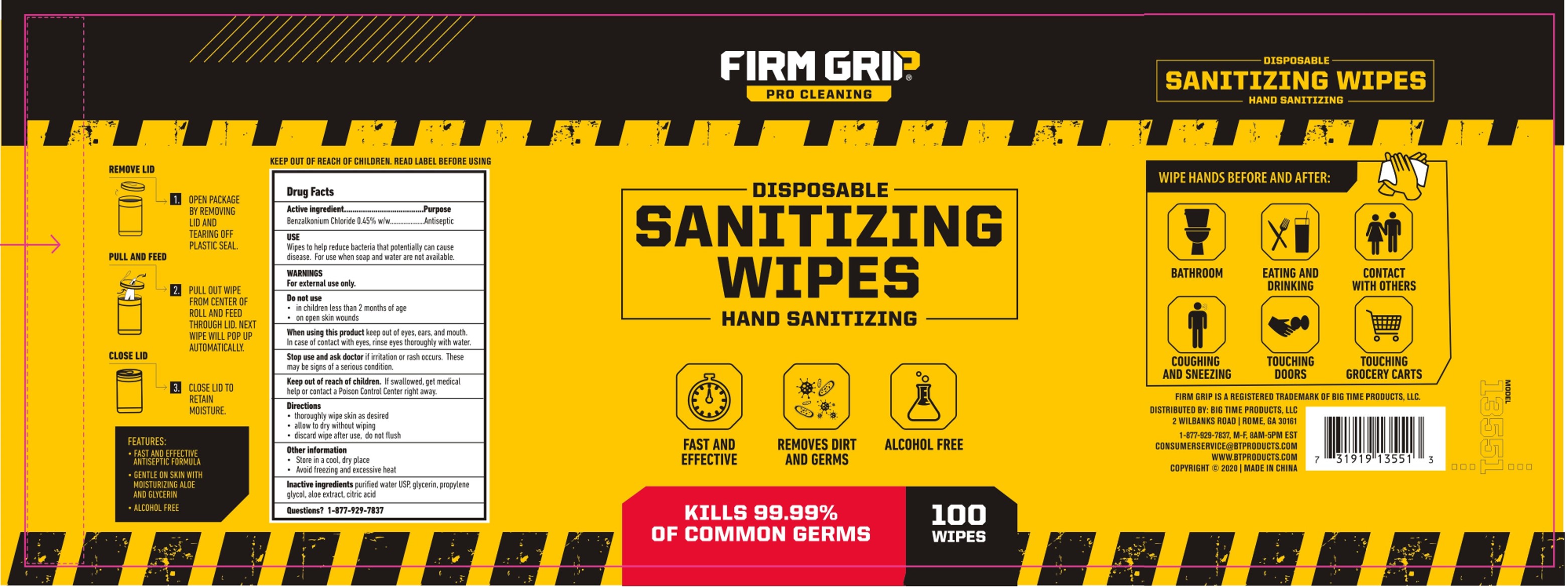 DRUG LABEL: SANITIZING WIPES
NDC: 80748-529 | Form: CLOTH
Manufacturer: Big Time Products, Llc
Category: otc | Type: HUMAN OTC DRUG LABEL
Date: 20211208

ACTIVE INGREDIENTS: BENZALKONIUM CHLORIDE 0.45 g/100 g
INACTIVE INGREDIENTS: ALOE; ANHYDROUS CITRIC ACID; GLYCERIN; PROPYLENE GLYCOL; WATER

Active Ingredient(s)

Benzalkonium Chloride 0.45% w/w. Purpose: Antiseptic

Purpose

Antiseptic, Hand Sanitizer

Use

Wipes to help reduce bacteria that potentially can cause disease. For use when soap and water are not available.

Warnings

For external use only. Flammable. Avoid exposure to the sun.

Do not use

- in children less than 2 months of age
- on open skin wounds

When using this product keep out of eyes, ears, and mouth. In case of contact with eyes, rinse eyes thoroughly with water.
Stop use and ask a doctor if irritation or rash occurs. These may be signs of a serious condition.
Keep out of reach of children. If swallowed, get medical help or contact a Poison Control Center right away.

Stop use and ask a doctor if irritation or rash occurs. These may be signs of a serious condition.

Keep out of reach of children. If swallowed, get medical help or contact a Poison Control Center right away.

Directions

- thoroughly wipe skin as desired
- allow to dry without wiping
- discard wipe after use, do not flush

Other information

- Store between 15-30C (59-86F)
- Avoid freezing and excessive heat above 40C (104F)

Inactive ingredients

aloe extract, citric acid, glycerin, propylene glycol, purified water USP.

Package Label - Principal Display Panel

100 Wipes in 1 Pail NDC: 80748-529-03